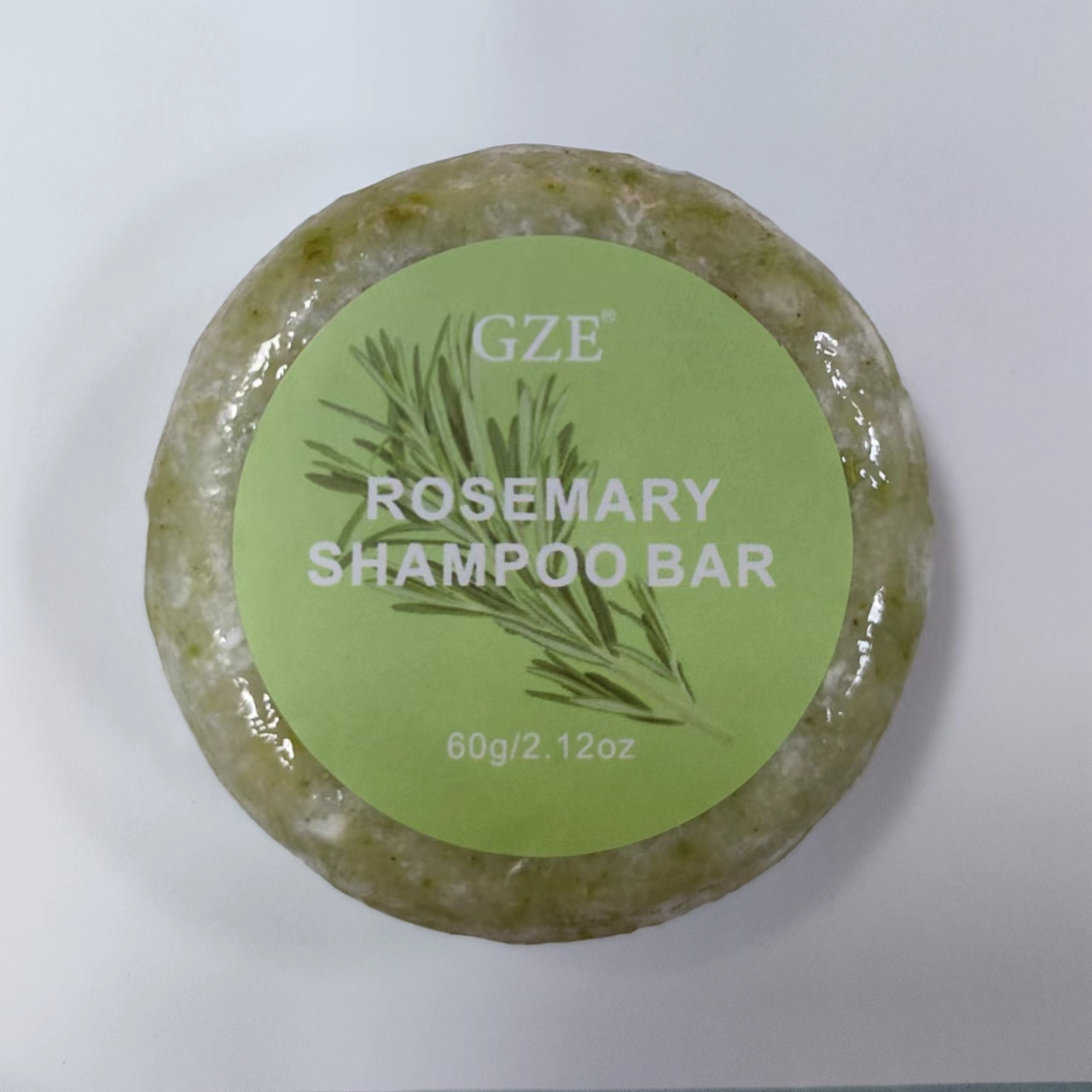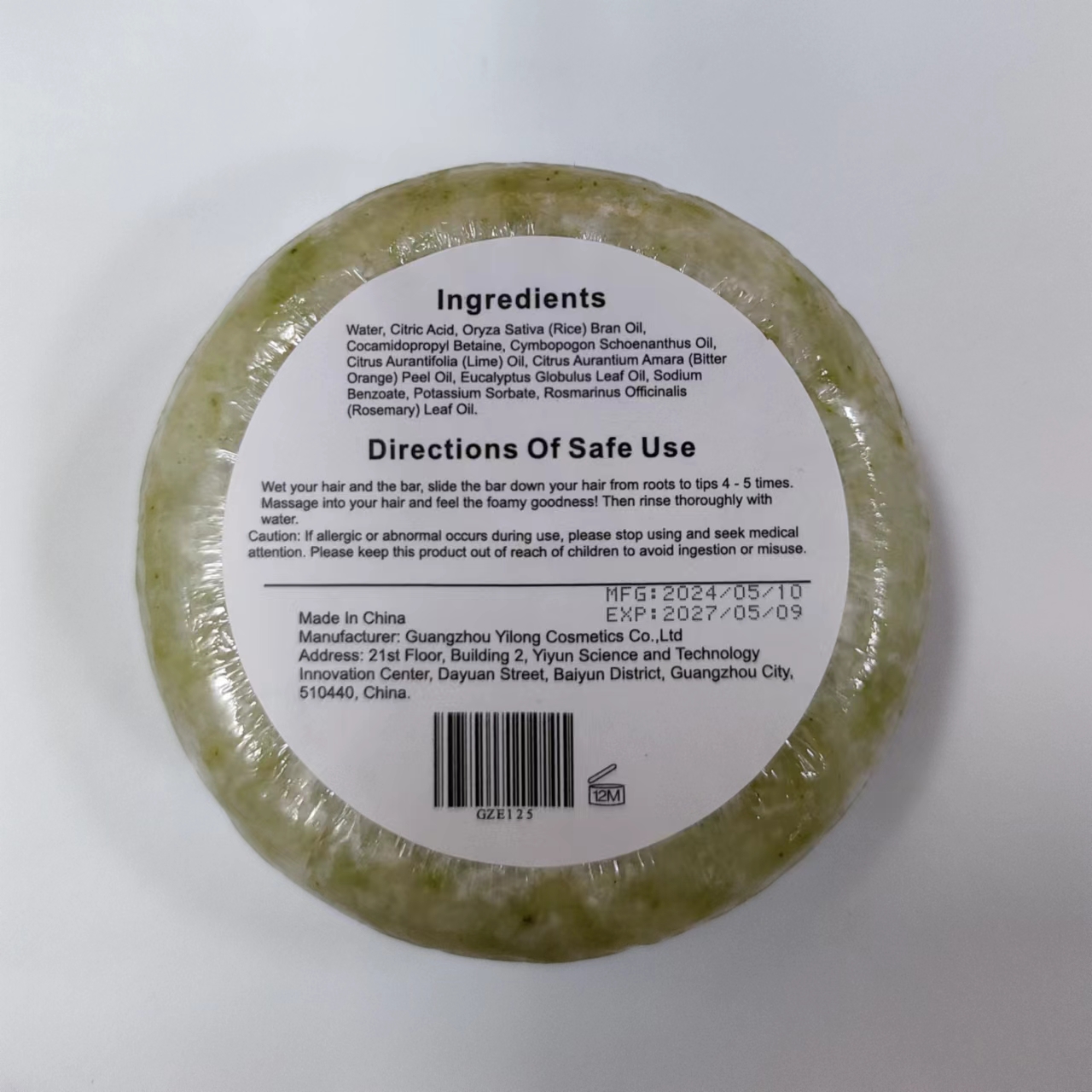 DRUG LABEL: GZE Rosemary ShampooBar
NDC: 83566-125 | Form: SOAP
Manufacturer: Guangzhou Yilong Cosmetics Co., Ltd
Category: otc | Type: HUMAN OTC DRUG LABEL
Date: 20240610

ACTIVE INGREDIENTS: ORYZA SATIVA WHOLE 10 g/60 g; EUCALYPTUS GLOBULUS LEAF 5 g/60 g; COCAMIDOPROPYL BETAINE 10 g/60 g; CITRUS AURANTIUM FRUIT OIL 5 g/60 g; ROSEMARY OIL 5 g/60 g; CITRUS AURANTIFOLIA SEED OIL 5 g/60 g; CYMBOPOGON SCHOENANTHUS OIL 5 g/60 g
INACTIVE INGREDIENTS: SODIUM BENZOATE; CITRIC ACID ACETATE; POTASSIUM SORBATE; WATER

GZE Rosemary ShampooBar

ACTIVE INGREDIENT

ORYZA SATIA WHOLE
CYMBOPOGON SCHOENANTHUS OIL
CITRUS AURANTIFOLIA SEED OIL
ROSEMARY OIL
CITRUS AURANTIUM FRUIT OIL
COCAMIDOPROPYL BETAINE
EUCALYPTUS GLOBULUS LEAF

PURPOSE

Cleanse scalp and hair.

INDICATIONS AND USAGE

Wet your hair and the bar, slide the bar down your hair from roots to tips 4 - 5 times. Massage into your hair and feel the foamy goodness! Then rinse thoroughly withwater.

WARNINGS

For external use only.

Stop use and ask a doctor if rash occurs.

Do not use on damaged or broken skin.

When using this product keep out of eyes. Rinse with water to remove.

Keep out of reach of children. If swallowed, get medical help or contact a Poison Control Center right away.

DOSAGE AND ADMINISTRATION

Wet your hair and the bar, slide the bar down your hair from roots to tips 4 - 5 times.Massage into your hair and feel the foamy goodness! Then rinse thoroughly with water.

INACTIVE INGREDIENT

SODIUM BENZOATE
CITRIC ACID ACETATE
POTASSIUM SORBATE
WATER